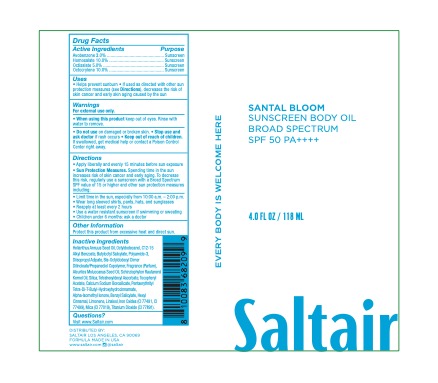 DRUG LABEL: SANTAL BLOOM SUNSCREEN BODY BROAD SPECTRUM SPF 50
NDC: 87290-001 | Form: OIL
Manufacturer: Saltair Body LLC
Category: otc | Type: HUMAN OTC DRUG LABEL
Date: 20260224

ACTIVE INGREDIENTS: AVOBENZONE 3 g/100 g; HOMOSALATE 10 g/100 g; OCTISALATE 5 g/100 g; OCTOCRYLENE 10 g/100 g
INACTIVE INGREDIENTS: HELIANTHUS ANNUUS WHOLE; OCTYLDODECANOL; C12-15 ALCOHOLS; BUTYLOCTYL SALICYLATE; POLYAMIDE-3 (30000 MW); DIISOPROPYL ADIPATE; BIS-OCTYLDODECYL DIMER DILINOLEATE/PROPANEDIOL COPOLYMER; ALEURITES MOLUCCANA SEED; SCHINZIOPHYTON RAUTANENII SEED OIL; TETRAHEXYLDECYL ASCORBATE; BENZYL SALICYLATE; MICA; TITANIUM DIOXIDE; FERRIC OXIDE; .ALPHA.-TOCOPHEROL ACETATE, D-; SILICA; CALCIUM SODIUM BOROSILICATE

SANTAL BLOOM SUNSCREEN BODY BROAD SPECTRUM SPF 50

Active Ingredients

Avobenzone 3.0%

Homosalate 10.0%

Octisalate 5.0%

Octocrylene 10.0%

Purpose

Purpose: Sunscreen

Uses

• helps prevent sunburn • if used as directed with other
sun protection measures (see Directions), decreases the
risk of skin cancer and early skin aging caused by the sun

Warnings

For external use only
Do not use on damaged or broken skin.
When using this product keep out of eyes. Rinse with water to remove.
Stop use and ask a docor if rash occurs
Keep out of reach of children. If swalled, get medical help or contact a Poison Control Center right away.

Keep out of reach of children. If product is swallowed, get medical help or contact a Poison Control Center right away.

Directions

• apply generously 15 minutes before sun exposure
• reapply: •at least every 2 hours.

• use a water resistant sunscreen if swimming or sweating
• Sun Protection Measures. Spending time in the sun

increases your risk of skin cancer and early skin aging. To decrease
this risk, regularly use a sunscreen with a Broad Spectrum SPF
value of 15 or higher and other sun protection measures including:
• limit time in the sun, especially from 10 a.m. - 2 p.m.
• wear long-sleeved shirts, pants, hats, and sunglasses
• children under 6 months of age: Ask a doctor

Inactive ingredients

Helianthus Annuus Seed Oil, Octyldodecanol, C12-15 Alkyl Benzoate, Butyloctyl Salicylate, Polyamide-3, Diisopropyl Adipate, Bis-Octyldecyl Dimer Dilinoleate/Propanediol Copolymer, Fragrance (Parfum), Aleurites Moluccanus Seed Oil, Schinziophyton Rautanenii Kernel Oil, Silica, Tetrahyexyldecyl Ascorbate, Tocopheryl Acetate, Calcium Sodium Borosilicate, Pentaerythrityl Tetra-Di-T-Butyl-Hydroxyhydrocinnamate, Alpha-Isomethyl Ionone, Benzyl Salicylate, Hexyl Cinnamate, Limonene, Linalool, Titanium Dioxide (CI 77891), Mica (CI 77019), Iron Oxides (CI 77499, CI 77491)

Other Information

• protect the product in this container from excessive
heat and direct sun

Questions?

Visit www.Saltair.com